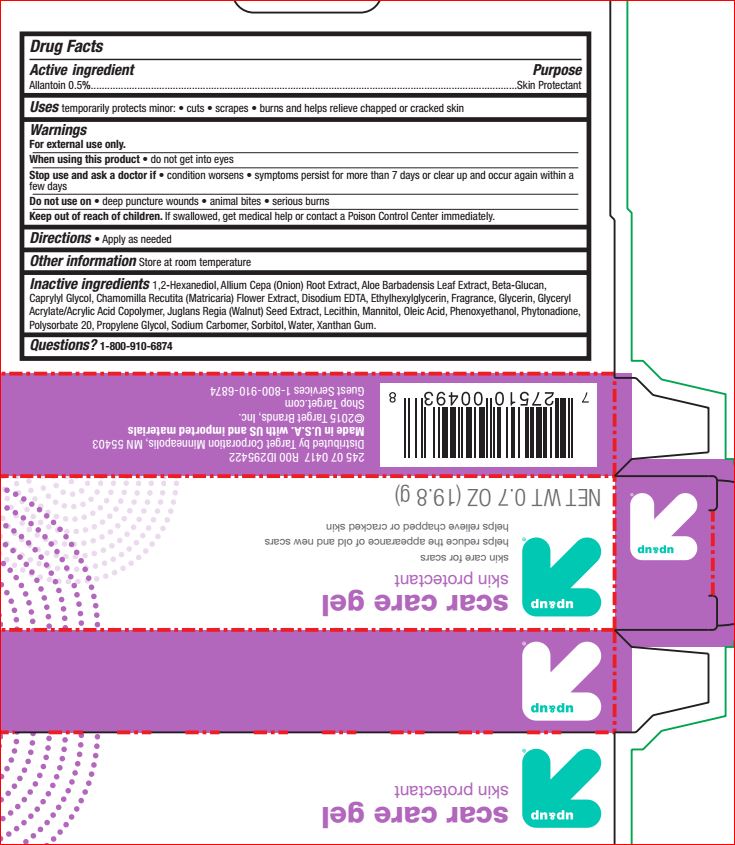 DRUG LABEL: Scar Care
NDC: 11673-777 | Form: GEL
Manufacturer: Target Corporation
Category: otc | Type: HUMAN OTC DRUG LABEL
Date: 20180703

ACTIVE INGREDIENTS: Allantoin 0.5 g/100 g
INACTIVE INGREDIENTS: ONION; Polysorbate 20; Sorbitol; Xanthan Gum; Oleic Acid; ALOE VERA LEAF; ENGLISH WALNUT; CHAMOMILE; Caprylyl Glycol; 1,2-Hexanediol; Ethylhexylglycerin; Phenoxyethanol; Phytonadione; WATER; EDETATE DISODIUM

Walgreens
Drug Facts

Active ingredient Purpose

Allantoin 0.5%........................Skin Protectant

INDICATIONS AND USAGE

Uses temporarily protects and helps relieve chapped or cracked skin

When using this product • do not get into eyes

Stop use and ask a doctor if • condition worsens • symptoms persist for more than 7 days or clear up and occur again within a few days

Do not use on • deep puncture wounds • animal bites • serious burns

Keep out of reach of children. If swallowed,get medical help or contact a Poison Control Center immediately

DOSAGE AND ADMINISTRATION

Directions • Apply as needed

Inactive ingredients
Water, Glycerin, Glyceryl Acrylate/Acrylic Acid
Copolymer, Propylene Glycol, Allium Cepa
(Onion) Root Extract, Polysorbate 20, Sorbitol,
Lecithin, Xanthan Gum, Oleic Acid,
Beta-Glucan, Sodium Carbomer, Aloe
Barbadensis Leaf Extract, Juglans Regia
(Walnut) Seed Extract, Chamomilla Recutita
(Matricaria) Flower Extract, Fragrance,
Caprylyl Glycol, 1,2-Hexanediol,
Ethylhexylglycerin, Phenoxyethanol, Disodium
EDTA, Phytonadione.

Other information Store at room temperature